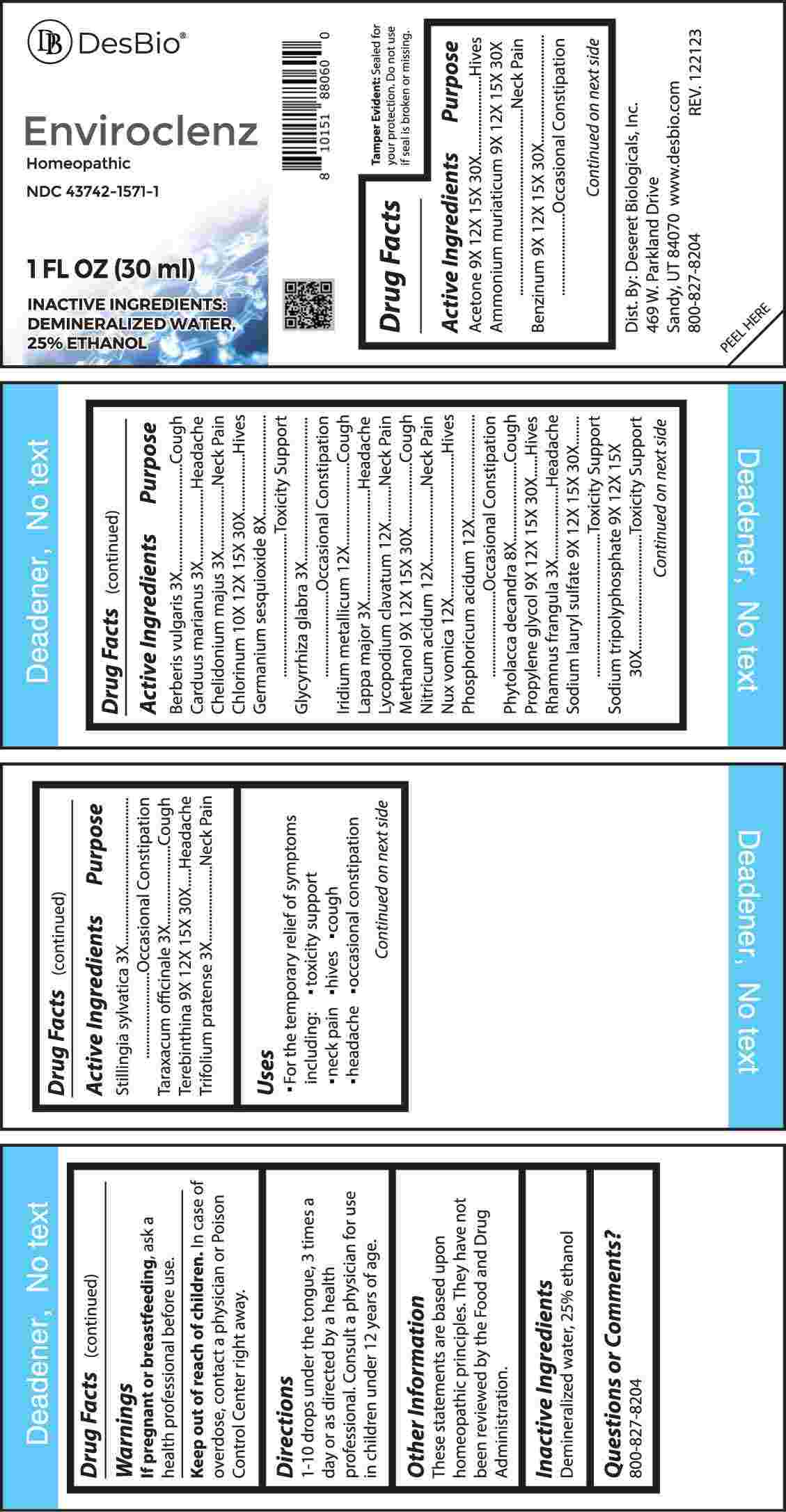 DRUG LABEL: Enviroclenz
NDC: 43742-1571 | Form: LIQUID
Manufacturer: Deseret Biologicals, Inc.
Category: homeopathic | Type: HUMAN OTC DRUG LABEL
Date: 20240502

ACTIVE INGREDIENTS: BERBERIS VULGARIS ROOT BARK 3 [hp_X]/1 mL; MILK THISTLE 3 [hp_X]/1 mL; CHELIDONIUM MAJUS WHOLE 3 [hp_X]/1 mL; GLYCYRRHIZA GLABRA 3 [hp_X]/1 mL; ARCTIUM LAPPA ROOT 3 [hp_X]/1 mL; FRANGULA ALNUS BARK 3 [hp_X]/1 mL; STILLINGIA SYLVATICA ROOT 3 [hp_X]/1 mL; TARAXACUM OFFICINALE FLOWERING TOP 3 [hp_X]/1 mL; TRIFOLIUM PRATENSE LEAF 3 [hp_X]/1 mL; GERMANIUM SESQUIOXIDE 8 [hp_X]/1 mL; PHYTOLACCA AMERICANA ROOT 8 [hp_X]/1 mL; ACETONE 9 [hp_X]/1 mL; AMMONIUM CHLORIDE 9 [hp_X]/1 mL; BENZENE 9 [hp_X]/1 mL; PROPYLENE GLYCOL 9 [hp_X]/1 mL; SODIUM LAURYL SULFATE 9 [hp_X]/1 mL; SODIUM TRIPOLYPHOSPHATE 9 [hp_X]/1 mL; TURPENTINE OIL 9 [hp_X]/1 mL; METHYL ALCOHOL 9 [hp_X]/1 mL; CHLORINE 10 [hp_X]/1 mL; IRIDIUM 12 [hp_X]/1 mL; LYCOPODIUM CLAVATUM SPORE 12 [hp_X]/1 mL; NITRIC ACID 12 [hp_X]/1 mL; STRYCHNOS NUX-VOMICA SEED 12 [hp_X]/1 mL; PHOSPHORIC ACID 12 [hp_X]/1 mL
INACTIVE INGREDIENTS: WATER; ALCOHOL

DRUG FACTS:

ACTIVE INGREDIENTS:

Acetone 9X, 12X, 15X, 30X, Ammonium Muriaticum 9X, 12X, 15X, 30X, Benzinum 9X, 12X, 15, 30X, Berberis Vulgaris 3X, Carduus Marianus 3X, Chelidonium Majus 3X, Chlorinum 10X, 12X, 15X, 30X, Germanium Sesquioxide 8X, Glycyrrhiza Glabra 3X, Iridium Metallicum 12X, Lappa Major 3X, Lycopodium Clavatum 12X, Methanol 9X, 12X, 15X, 30X, Nitricum Acidum 12X, Nux Vomica 12X, Phosphoricum Acidum 12X, Phytolacca Decandra 8X, , Propylene Glycol 9X, 12X, 15X, 30X, Rhamnus Frangula 3X, Sodium Lauryl Sulfate 9X, 12X, 15X, 30X, Sodium Tripolyphosphate 9X, 12X, 15X, Stillingia Sylvatica 3X, Taraxacum Officinale 3X, Terebinthina 9X, 12X, 15X, 30X, Trifolium Pratense 3X, 30X.

PURPOSE:

Acetone - Hives, Ammonium Muriaticum – Neck Pain, Benzinum – Occasional Constipation, Berberis Vulgaris - Cough, Carduus Marianus - Headache, Chelidonium Majus – Neck Pain, Chlorinum - Hives, Germanium Sesquioxide – Toxicity Support, Glycyrrhiza Glabra – Occasional Constipation, Iridium Metallicum - Cough, Lappa Major - Headache, Lycopodium Clavatum – Neck Pain, Methanol - Cough, Nitricum Acidum – Neck Pain, Nux Vomica - Hives, Phosphoricum Acidum – Occasional Constipation, Phytolacca Decandra - Cough, Propylene Glycol - Hives, Rhamnus Frangula - Headache, Sodium Lauryl Sulfate – Toxicity Support, Sodium Tripolyphosphate – Toxicity Support, Stillingia Sylvatica – Occasional Constipation, Taraxacum Officinale - Cough, Terebinthina - Headache, Trifolium Pratense – Neck Pain

USES:

• For the temporary relief of symptoms including:

• toxicity support • neck pain • hives • cough

• headache • occasional constipation

These statements are based upon homeopathic principles. They have not been reviewed by the Food and Drug Administration.

WARNINGS:

If pregnant or breast-feeding, ask a health professional before use.

Keep out of reach of children. In case of overdose, contact a physician or Poison Control Center right away.
Tamper Evident: Sealed for your protection. Do not use if seal is broken or missing.

KEEP OUT OF REACH OF CHILDREN:

In case of overdose, contact a physician or Poison Control Center right away.

DIRECTIONS:

1-10 drops under the tongue, 3 times a day or as directed by a health professional. Consult a physician for use in children under 12 years of age.

INACTIVE INGREDIENTS:

Demineralized Water, 25% ethanol

QUESTIONS:

Dist. By: Deseret Biologicals, Inc.
469 W. Parkland Drive
Sandy, UT 84070

www.desbio.com

800-827-8204

PACKAGE LABEL DISPLAY:

Des Bio

Enviroclenz

Homeopathic
NDC 43742-1571-1
1 FL OZ (30 ml